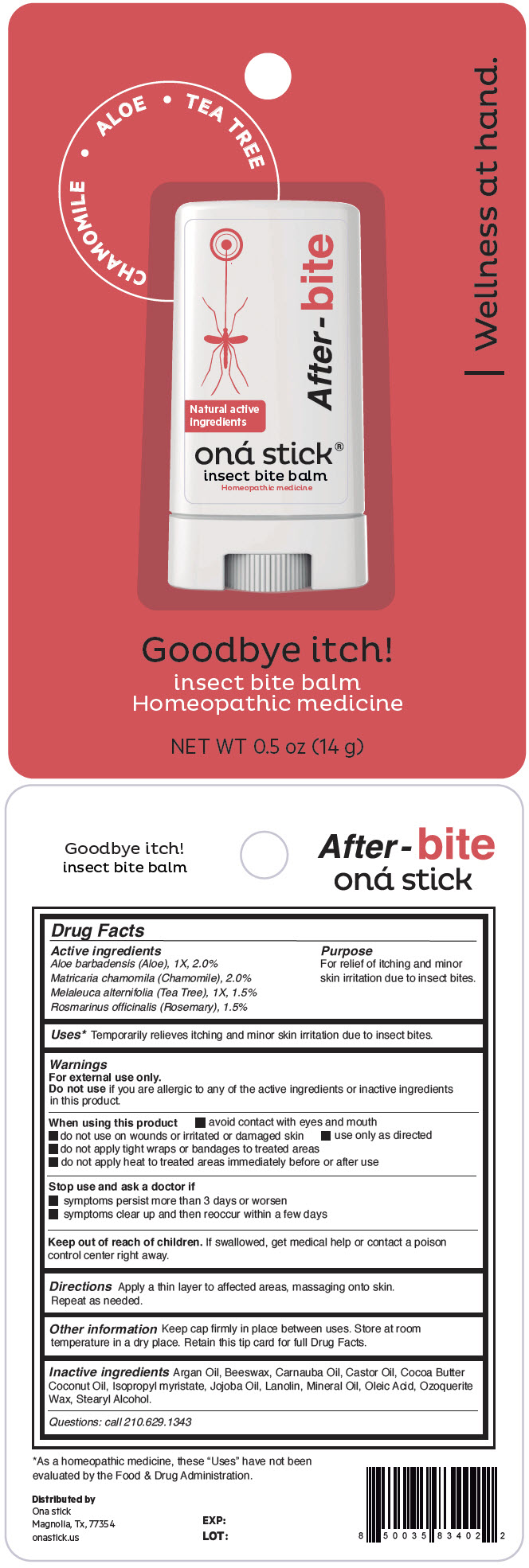 DRUG LABEL: After-bite
NDC: 82610-002 | Form: STICK
Manufacturer: ONA STICK USA LLC
Category: homeopathic | Type: HUMAN OTC DRUG LABEL
Date: 20220318

ACTIVE INGREDIENTS: ALOE VERA LEAF 1 [hp_X]/14 g; MATRICARIA CHAMOMILLA WHOLE 1 [hp_X]/14 g; MELALEUCA ALTERNIFOLIA LEAF 1 [hp_X]/14 g; ROSEMARY 1 [hp_X]/14 g
INACTIVE INGREDIENTS: Argan Oil; YELLOW WAX; CARNAUBA WAX; Castor Oil; Cocoa Butter; Coconut Oil; Isopropyl Myristate; Jojoba Oil; Lanolin; Mineral Oil; Oleic Acid; CERESIN; Stearyl Alcohol

After-bite

Drug Facts

ACTIVE INGREDIENT

Active ingredients | Purpose
Aloe barbadensis (Aloe), 1X, 2.0% Matricaria chamomila (Chamomile), 2.0% Melaleuca alternifolia (Tea Tree), 1X, 1.5% Rosmarinus officinalis (Rosemary), 1.5% | For relief of itching and minor skin irritation due to insect bites.

Uses [As a homeopathic medicine, these "Uses" have not been evaluated by the Food & Drug Administration.]

Temporarily relieves itching and minor skin irritation due to insect bites.

Warnings

For external use only.

Do not use if you are allergic to any of the active ingredients or inactive ingredients in this product.

When using this product

- avoid contact with eyes and mouth
- do not use on wounds or irritated or damaged skin
- use only as directed
- do not apply tight wraps or bandages to treated areas
- do not apply heat to treated areas immediately before or after use

Stop use and ask a doctor if

- symptoms persist more than 3 days or worsen
- symptoms clear up and then reoccur within a few days

Keep out of reach of children. If swallowed, get medical help or contact a poison control center right away.

Directions

Apply a thin layer to affected areas, massaging onto skin. Repeat as needed.

Other information

Keep cap firmly in place between uses. Store at room temperature in a dry place. Retain this tip card for full Drug Facts.

Inactive ingredients

Argan Oil, Beeswax, Carnauba Oil, Castor Oil, Cocoa Butter Coconut Oil, Isopropyl myristate, Jojoba Oil, Lanolin, Mineral Oil, Oleic Acid, Ozoquerite Wax, Stearyl Alcohol.

Questions

call 210.629.1343

Distributed by
Ona stick
Magnolia, Tx, 77354

PRINCIPAL DISPLAY PANEL - 14 g Tube Blister Pack

CHAMOMILE • ALOE • TEA TREE

Natural active
ingredients

After-bite

oná stick®
insect bite balm
Homeopathic medicine

| Wellness at hand.

Goodbye itch!

insect bite balm
Homeopathic medicine

NET WT 0.5 oz (14 g)